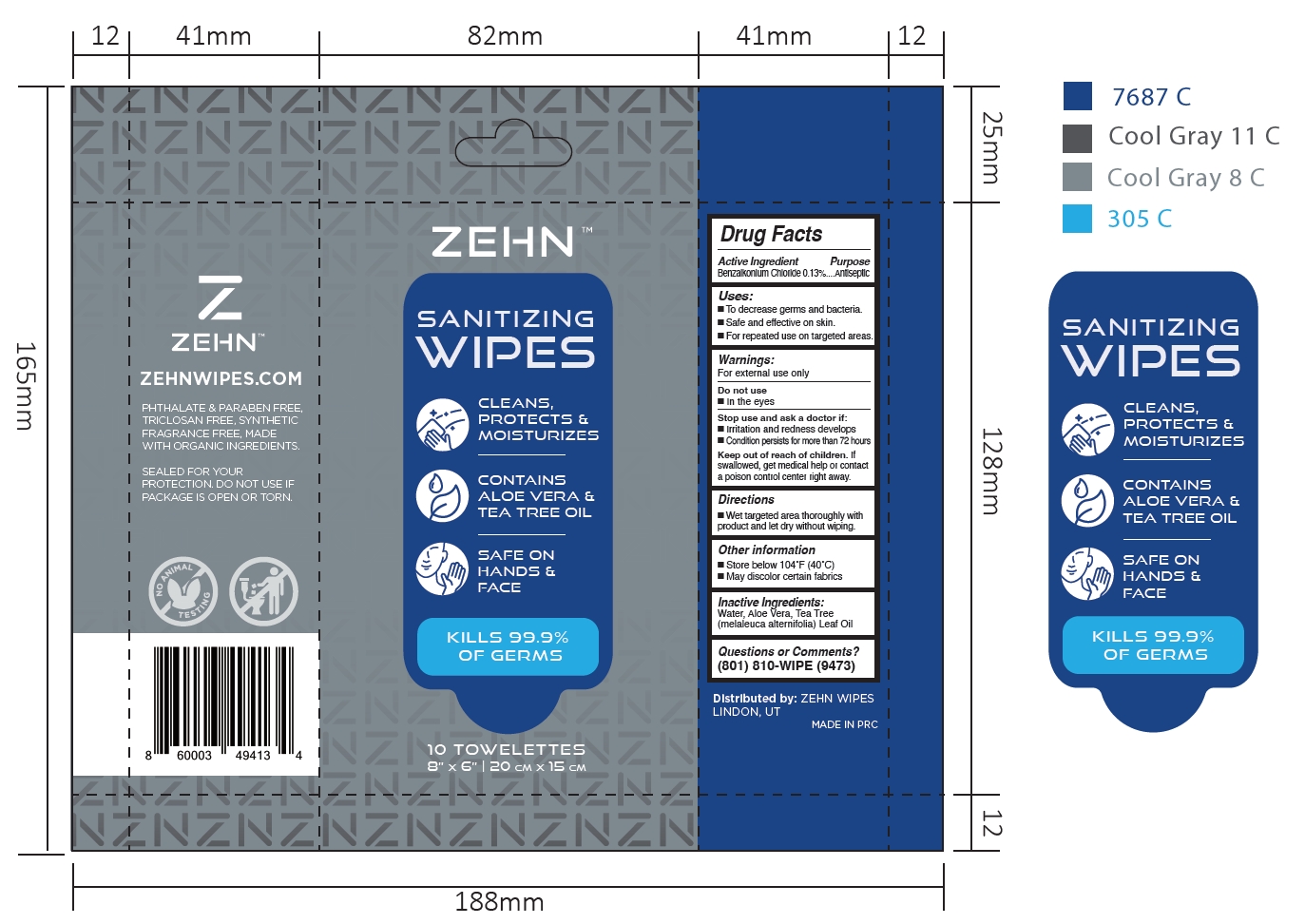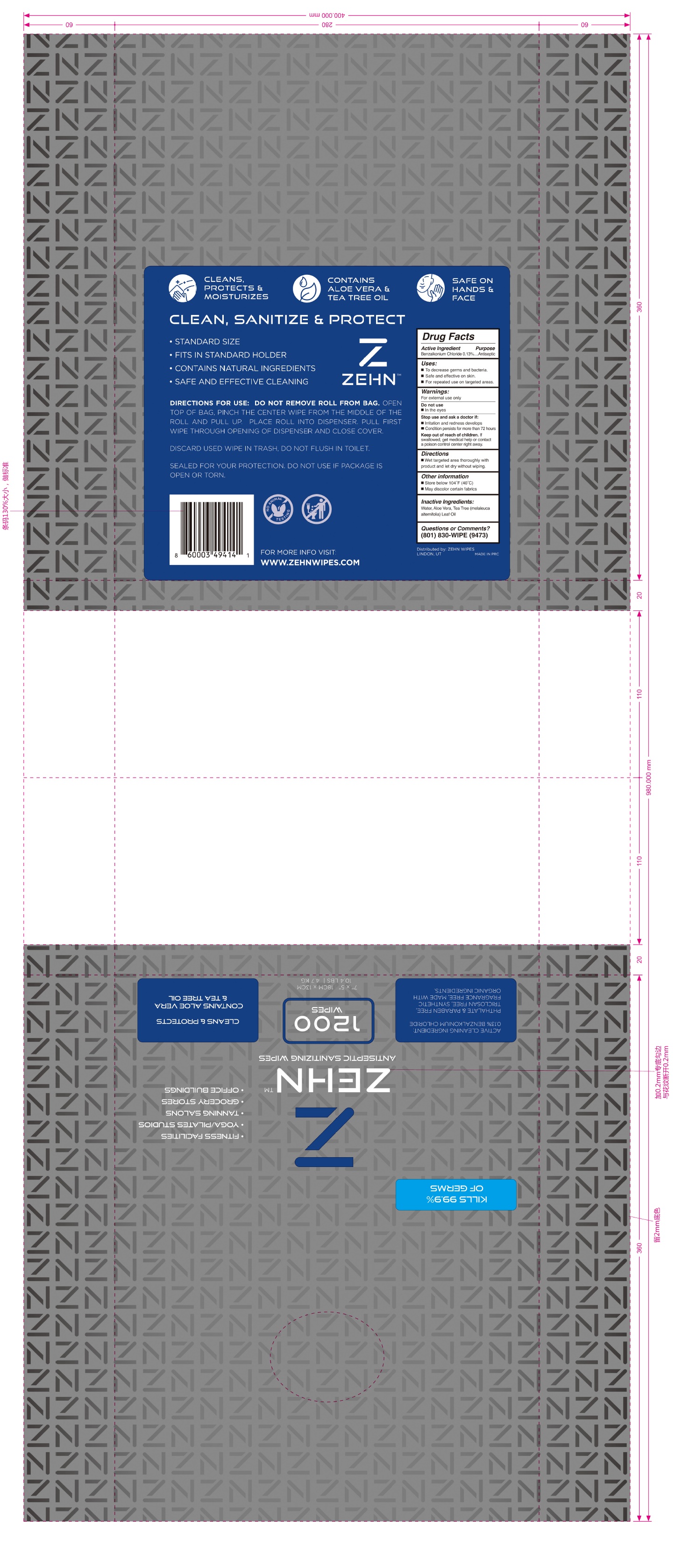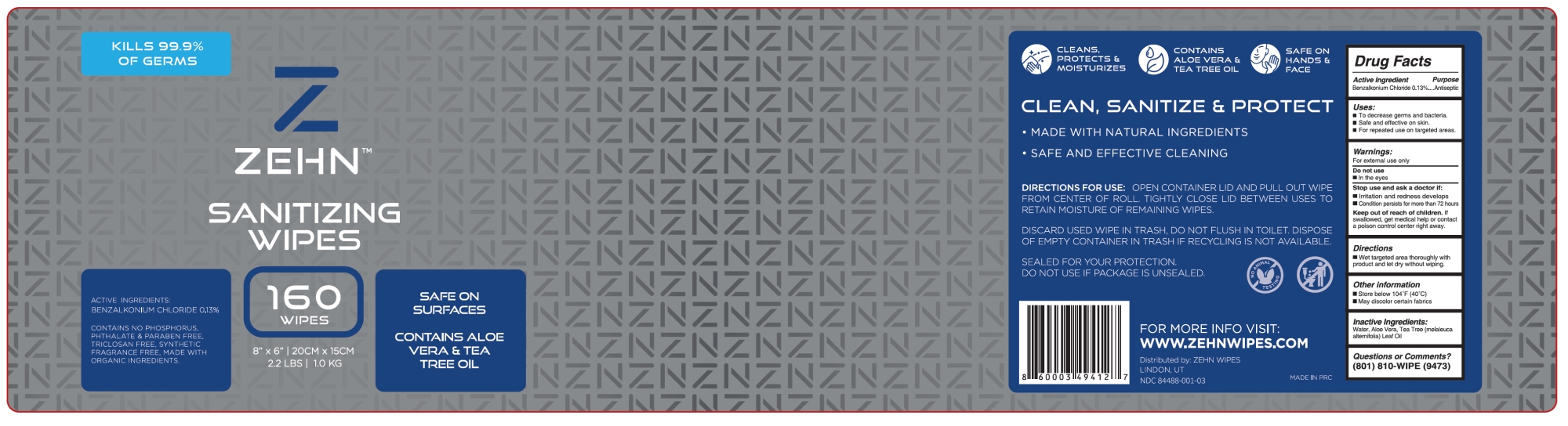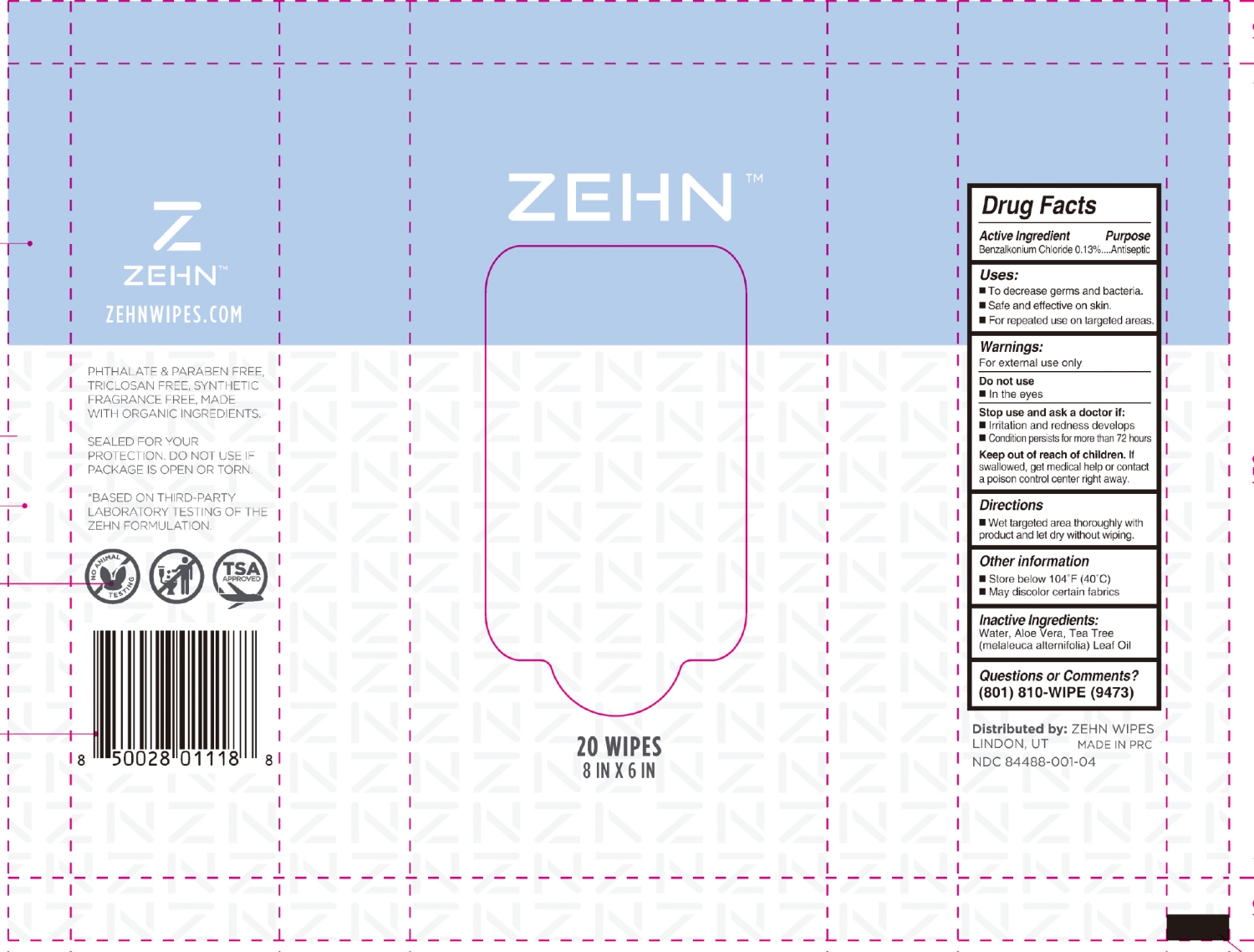 DRUG LABEL: Zehn Antiseptic Sanitizing Wipes
NDC: 84488-001 | Form: CLOTH
Manufacturer: Zehn Wipes
Category: otc | Type: HUMAN OTC DRUG LABEL
Date: 20260204

ACTIVE INGREDIENTS: BENZALKONIUM CHLORIDE 0.13 g/100 g
INACTIVE INGREDIENTS: ALOE VERA LEAF; WATER; MELALEUCA ALTERNIFOLIA (TEA TREE) LEAF OIL

84488-001 Zehn Antiseptic Sanitizing Wipes

Active Ingredient

Benzalkonium Chloride 0.13 %

Purpose

Antiseptic

Uses:

■ To decrease germs and bacteria.

■ Safe and effective on skin.

■ For repeated use on targeted areas.

Warnings:

For external use only.

Do not use

■ In the eyes

Stop use and ask a doctor if:

■ Irritation and redness develops

■ Condition persists for more than 72 hours

Keep out of reach of children. If

swallowed, get medical help or contact

a poison control center right away.

Directions

■ Wet targeted area thoroughly with

product and let dry without wiping.

Other information

■ Store below 104˚F (40˚C)

■ May discolor certain fabrics

Inactive Ingredients:

Water, Aloe Vera, Tea Tree

(melaleuca alternifolia) Leaf Oil

PACKAGE LABEL

10 TOWELETTES
NDC: 84488-001-01

PACKAGE LABEL

1200 WIPES
NDC: 84488-001-02

PACKAGE LABEL

160 WIPES
NDC: 84488-001-03

PACKAGE LABEL

20 WIPES
NDC: 84488-001-04